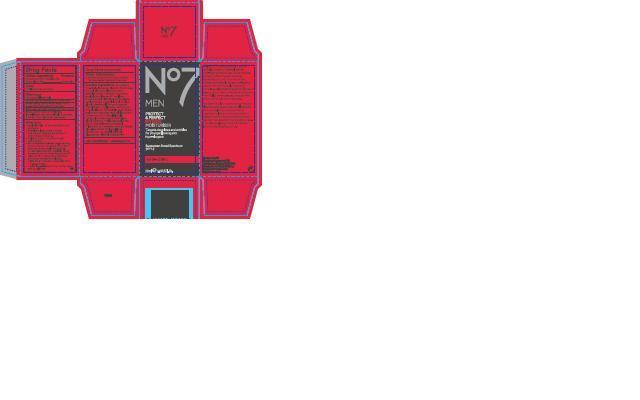 DRUG LABEL: No7 Men Protect and Perfect Intense Moisturiser
NDC: 11489-079 | Form: CREAM
Manufacturer: BCM Ltd
Category: otc | Type: HUMAN OTC DRUG LABEL
Date: 20121210

ACTIVE INGREDIENTS: AVOBENZONE 1.5 g/50 g; OCTISALATE 1.5 g/50 g; OCTOCRYLENE 2 g/50 g
INACTIVE INGREDIENTS: WATER; C12-15 ALKYL BENZOATE; GLYCERIN; DIMETHICONE; CETEARYL GLUCOSIDE; ALUMINUM STARCH OCTENYLSUCCINATE; TRIBEHENIN; AMMONIUM ACRYLOYLDIMETHYLTAURATE/VP COPOLYMER; PHENOXYETHANOL; POTASSIUM CETYL PHOSPHATE; CETOSTEARYL ALCOHOL; BUTYLENE GLYCOL; DIMETHICONOL (100000 CST); METHYLPARABEN; ETHYLPARABEN; XANTHAN GUM; VITAMIN A PALMITATE; ASCORBYL GLUCOSIDE; EDETATE SODIUM; LUPINUS ALBUS SEED; DIPROPYLENE GLYCOL; PHYLLANTHUS EMBLICA FRUIT; POLYSORBATE 20; POTASSIUM HYDROXIDE; ETHYLHEXYLGLYCERIN; TOCOPHEROL; PALMITOYL OLIGOPEPTIDE; PALMITOYL TETRAPEPTIDE-7

No7 Men Protect and Perfect Intense Moisturiser

Warnings

For external use only

Do not use on damaged or broken skin

When using this product keep out of eyes. Rinse with water to remove

Ask a doctor

Stop use and ask a doctor if rash occurs

Keep out of reach of children. If swallowed, get medical help or contact a Poison Center right away

Directions

Directions for sunscreen use

apply liberally 15 minutes before sun exposure

reapply at least every 2 hours

use a water resistant sunscreen if swimming or sweating

children under 6 months of age: Ask a doctor

Sun Protection Measures. Spending time in the sun increases your risk of skin cancer and eraly skin aging. Todecrease this risk, regularly use a sunscreen with a Broad spectrum SPF value of 15 or higher and other sun protection measures including:

limit time in the sun,especially from 10 a.m. - 2 p.m.

wear long-sleeved shirts, pants,hats, and sunglasses

Storage

Other information - protect the product in this container from excessive heat and direct sun

Inactive ingredients

Aqua (Water), C12-15 alkyl benzoate, Glycerin, Dimethicone, Cetearyl glucoside, Aluminum starch octenylsuccinate, Tribehenin, Ammonium acryloydimethyltaurate/VP copolymer, Phenoxyethanol, Alcohol denat., Potassium cetyl phosphate, Cetearyl alcohol, Butylene glycol, Dimethiconol, Parfum (Fragrance), Methylparaben,Ethylparaben, Xanthan gum, Retinyl palmitate, Ascorbyl glucoside, Sodium hyaluronate,Medicago sativa (Alfalfa) extract, Tetrasodium EDTA, T-butyl-alcohol, Lupinus seed extract, Dipropylene glycol, carbomer, Phyllanthus emblica fruit extract, Dimethylmethoxy chromanol, Polysorbate 20, Potassium hydroxide, Ginkgo biloba leaf extract, Ethylhexylglycerin, Simethicone, Tocopherol, Palmitoyl oligopeptide, Palmitoyl tetrapeptide-7

Description

Feeling confident about your skin is critical. Protect and Perfect Intense Anti-Ageing Moisturiser combines the unique protecting and renewing ingredients found in our renowned Protect & Perfect Intense Anti-Ageing Serum with an intensively hydrating complex. Helps defend against premature ageing from UVA and UVB rays and boosts skin vitality when used as directed with other sun protection measures.

For Best Results: Use every morning on clean skin. Squeeze out a small amount into your palm and rub your hands together to leave an even amount on each. Smooth into your face and neck paying more attention to the drier areas. Use after applying Protect and Perfect Intense Anti-Ageing serum

Information

Made in the UK

The Boots Company PLC

Nottingham England NG2 3AA

Dist. by Boots Retail USA Inc,

Norwalk CT 06851 USA

www.boots.com

Carton Active Ingredients Section

Active Ingredients

Avobenzone 3%

Octisalate 3%

Octocrylene 4%

Purpose Sunscreen

Uses

Uses - helps prevent sunburn

airless bottle with pump

No7 Men Protect and Perfect Intense Moisturiser Sunscreen Broad Spectrum SPF 15

50ml e 1.69 US Fl.Oz.

Active ingredients: Avobenzone 3%, Octisalate 3%, Octocrylene 4%

Warning

Avoid contact with eyes. If product gets into the eyes rinse well with water immediately.

Description

For Best Results: Use every morning on clean skin. Squeeze out a small amount into your palm and rub your hands together to leave an even amount on each. Smooth into your face and neck paying more attention to the drier areas. Use after applying Protect and Perfect Intense Anti-Age serum. Helps protect against the ageing effects of the sun when used as directed with other sun protection measures.

Information

The Boots Company PLC

Nottingham England NG2 3AA

Dist by Boots Retail USA Inc.

Norwalk CT 06851 USA

Made in the UK

www.boots.com

PACKAGE LABEL

carton